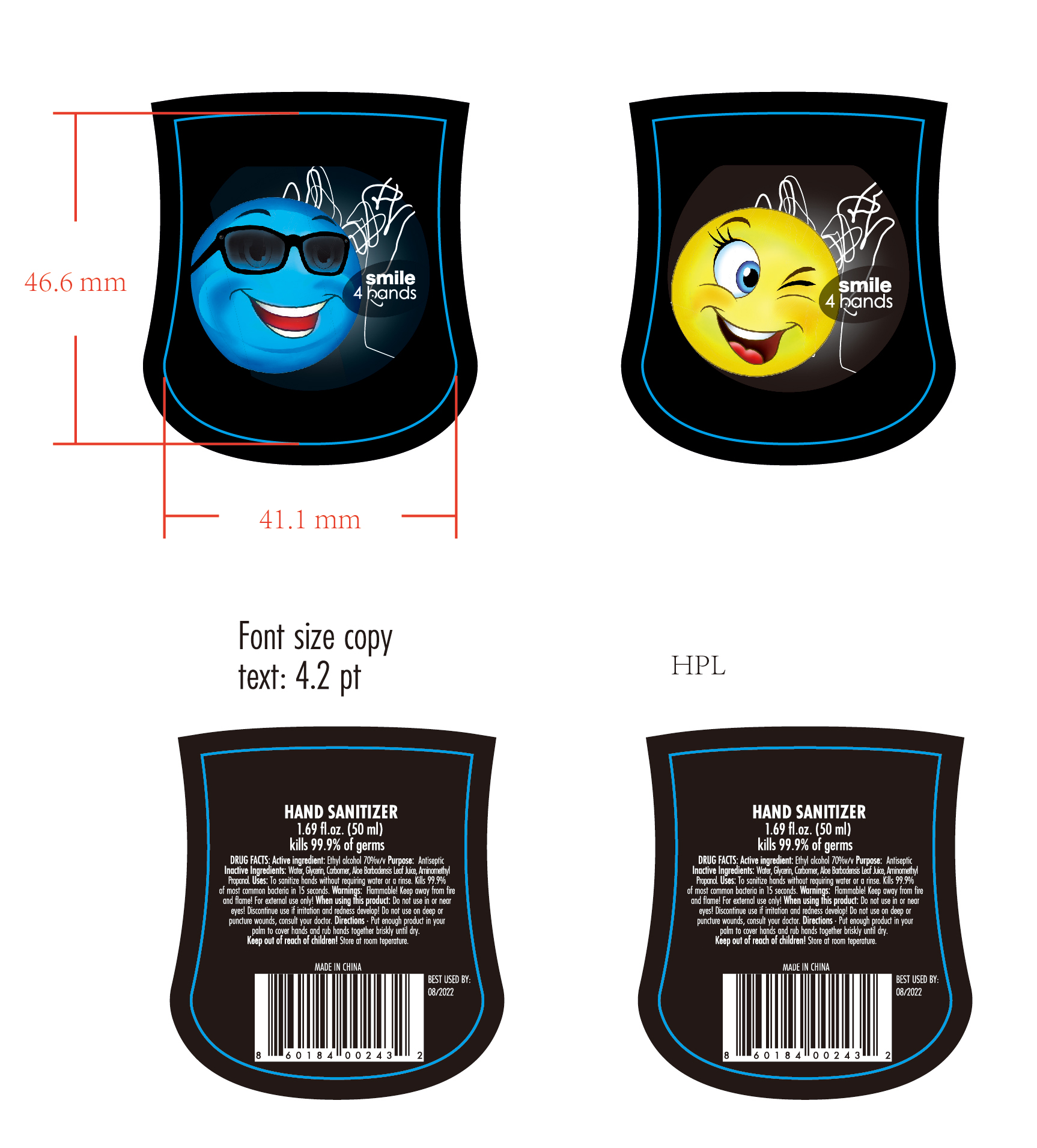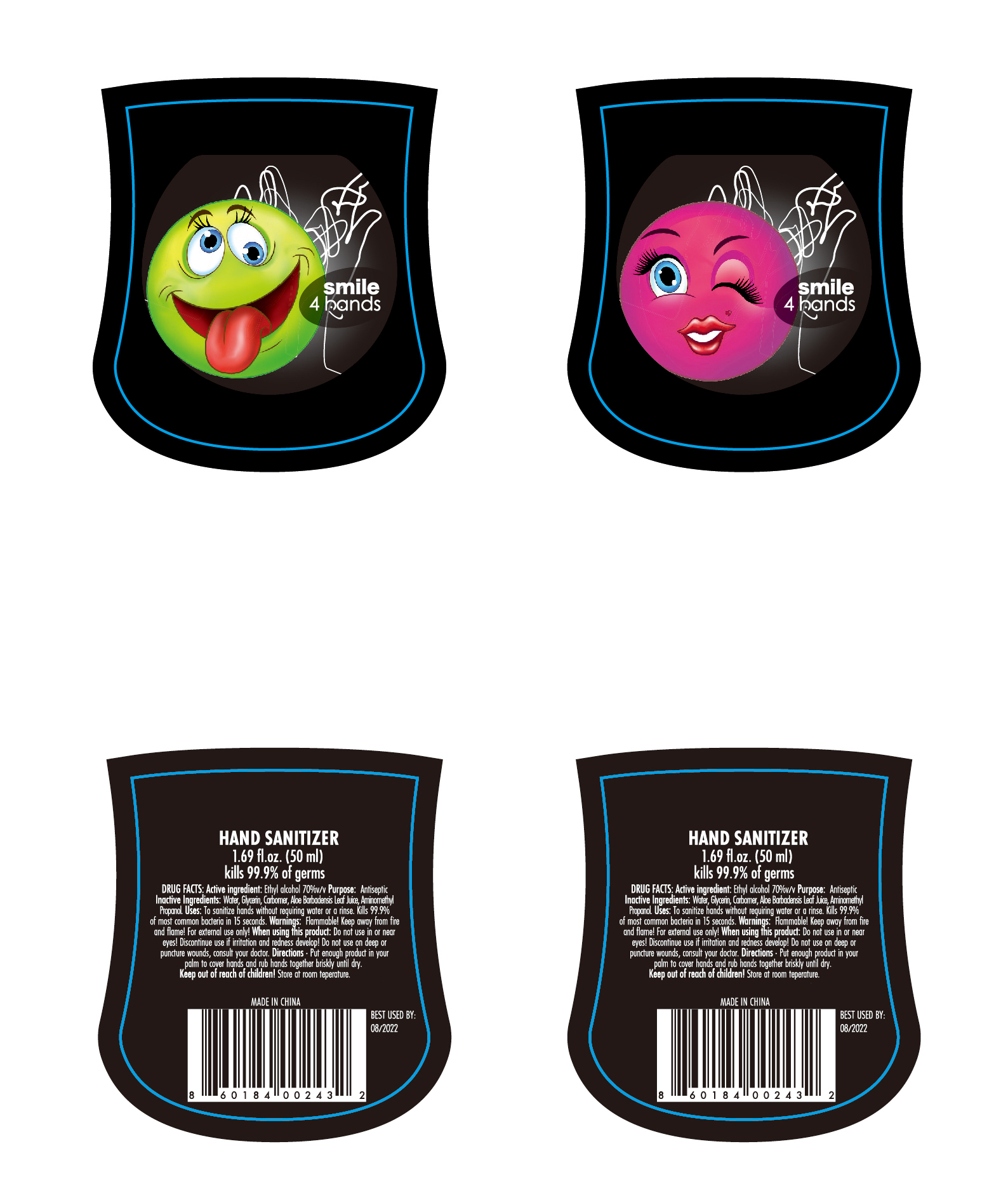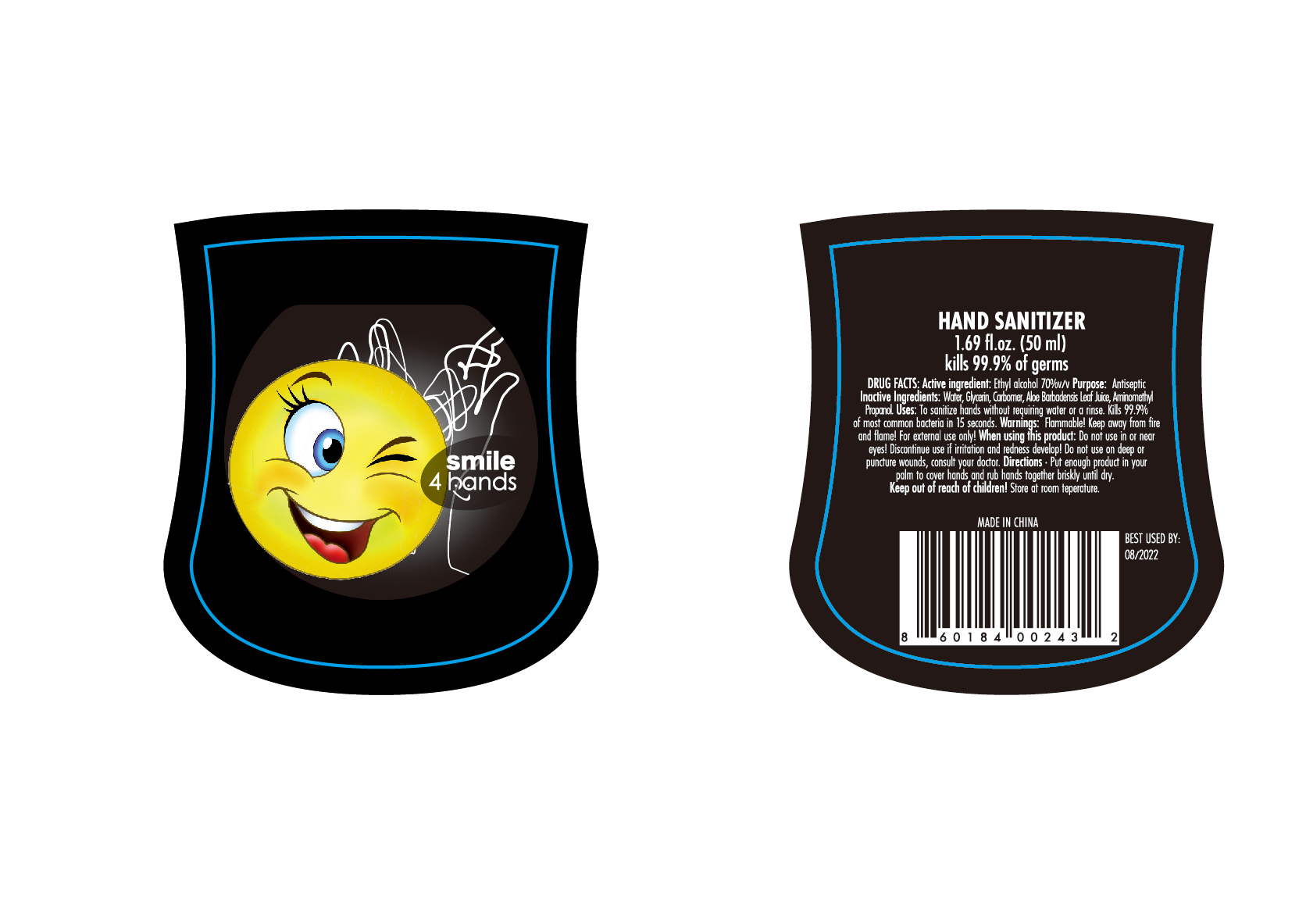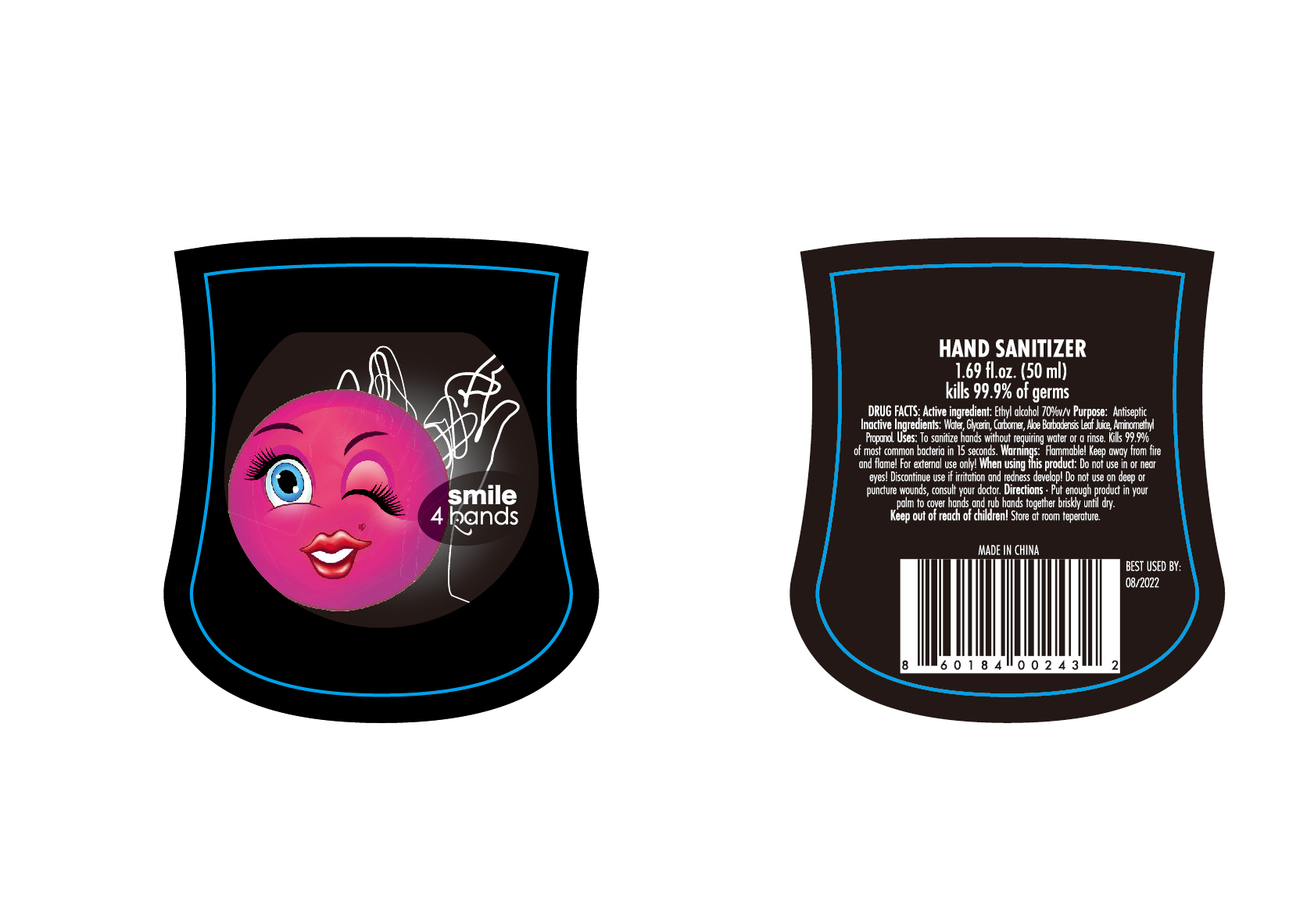 DRUG LABEL: HAND SANITIZER
NDC: 47993-315 | Form: GEL
Manufacturer: NINGBO JIANGBEI OCEAN STAR TRADING CO.,LTD
Category: otc | Type: HUMAN OTC DRUG LABEL
Date: 20201105

ACTIVE INGREDIENTS: ALCOHOL 70 mL/100 mL
INACTIVE INGREDIENTS: WATER; GLYCERIN; CARBOMER 940; ALOE VERA LEAF; AMINOMETHYLPROPANOL

47993-315

Active ingredients

Ethyl alcohol 70%v/v

PURPOSE

Antiseptic

Inactive Ingredients:

Water,Glycerin,Carbomer,Aloe Barbaensis Leaf Juice,Aminomethyl Propanol.

Uses：

To sanitize hands without requiring water or a rinse. Kills 99.9% of most common bacteria in 15 seconds.

Warnings:

Flammable! Keep away from fire or flame.For external use only.

When using this product：

Do not use in or near eyes！Discontinue use if irritation amd redness develop！Do not use on deep or puncture wounds, consult

your doctor.

Directions:

Put enough product in your palm to cover hands and rub hands together briskly until dry.

Keep out of reach of children!

OTHER SAFETY INFORMATION

Store at room teperature.